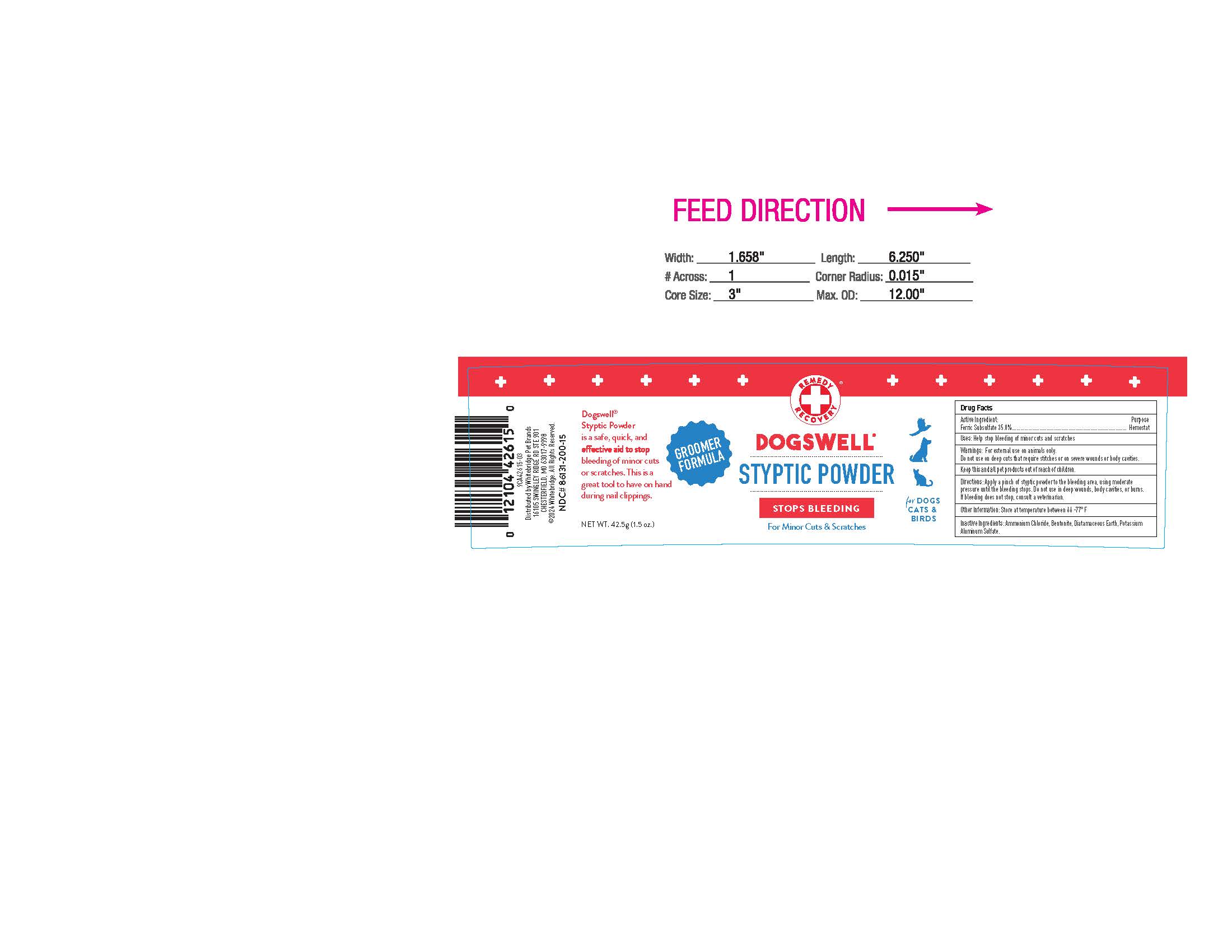 DRUG LABEL: Styptic Powder
NDC: 86131-200 | Form: POWDER
Manufacturer: Whitebridge Pet Brands
Category: animal | Type: OTC ANIMAL DRUG LABEL
Date: 20260123

ACTIVE INGREDIENTS: FERRIC SUBSULFATE 35 g/100 g
INACTIVE INGREDIENTS: BENTONITE; POTASSIUM SULFATE; DIATOMACEOUS EARTH; AMMONIUM CHLORIDE

Stypic Powder

Active Ingredients

Ferric Subsulfate 35.0%.....Hemostat

Uses:

Help stop bleeding of minor cuts and scratches.

Inactive Ingredients:

Ammonium Chloride, Bentonite, Diatamaceous Earth, Potassium Aluminum Sulfate.

Directions

Apply a pinch of styptic powder to the bleeding area, using moderte pressure until the bleeding stops. Do not use in deep wounds, body cavities, or burns. If bleeding does not stop, consult a veterinarian.

Warnings

For external use on animals only. Do not use on deep cuts that require stitches or on severe wounds or body cavities.

Keep this and all pet products out of reach of children.

STORAGE AND HANDLING

Store at temperature between 66-77 F

GROOMER FORMULA

Dogswell Styptic Powder is a safe, quick, and effective aid to stop bleeding of minor cuts or scratches. This is a great tool to have on habd during nail clipings.

Distributed by Whitebridge Pet Brands,

St. Louis, MO 63141

2020 Whitebridge. All Rights Reserved.

NDC# 86131-200-15

PACKAGE LABEL

Remedy Recovery

DOGSWELL

STYPTIC POWDER

STOPS BLEEDING

For Minor Cuts & Scratches

for DOGS CATS & BIRDS

NET WT. 42.5g (1.5 oz.)